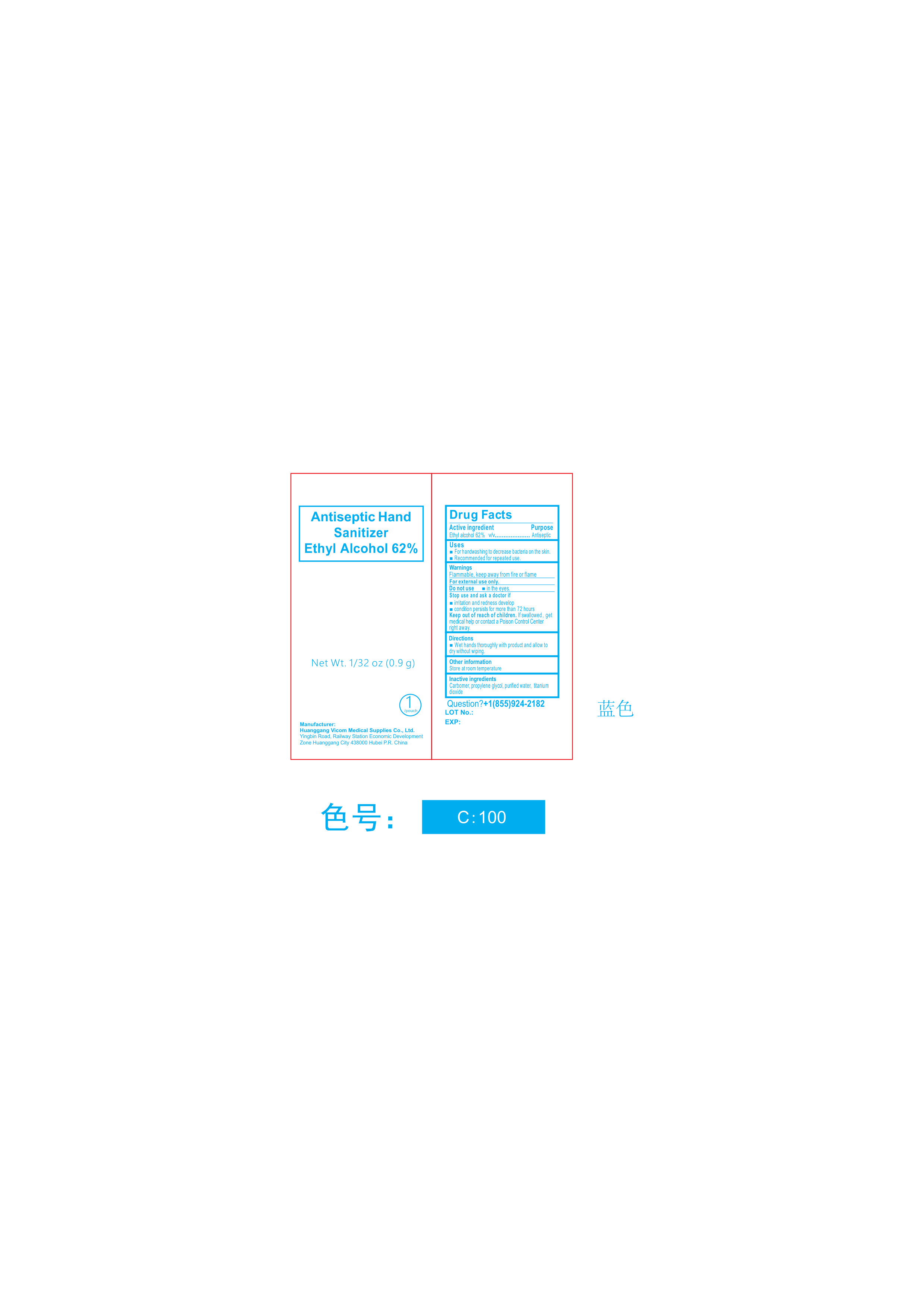 DRUG LABEL: Huanggang Antiseptic Hand Sanitizer
NDC: 85426-001 | Form: LIQUID
Manufacturer: Huanggang Vicom Medical Supplies Co., Ltd.
Category: otc | Type: HUMAN OTC DRUG LABEL
Date: 20250406

ACTIVE INGREDIENTS: ALCOHOL 62 mL/100 mL
INACTIVE INGREDIENTS: WATER; TITANIUM DIOXIDE; CARBOMER 934; PROPYLENE GLYCOL 1-ALLYL ETHER

Hand Sanitizer Huanggang Vicom Medical Supplies Co Ltd

WARNINGS

Flammable Keep Away from Fire and Flames

ACTIVE INGREDIENT

62% ETHYL ALCOHOL

ASK DOCTOR

when irritaiton and redness develop

condition persists for more than 72 hours

DO NOT USE

in the eyes

Keep out of reach of children. If swallowed get medical help or contact the Poison Control Center right away

PREGNANCY OR BREAST FEEDING

N/A

PURPOSE

For handwashing to decrease bacteria on the skin

reccomended for repeated use

QUESTIONS

For External Use Only

STOP USE

When you see redness or have irritation

WHEN USING

Wet hands thoroughly with product and allow to dry without wiping

OTHER SAFETY INFORMATION

Store at room tempature

INDICATIONS AND USAGE

Hand Sanitizer to help reduce bacteria that potentially can cause disease. For use when soap and water are not available.

DOSAGE AND ADMINISTRATION

Place enough product on hands to cover all surfaces. Rub hands together until dry.
Supervise children under 6 years of age when using this product to avoid swallowing.

INACTIVE INGREDIENT

Carbomer, Propylene Glycol, Purified Water, Titanium Dioxide